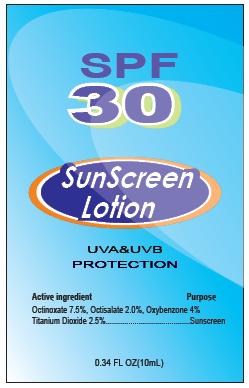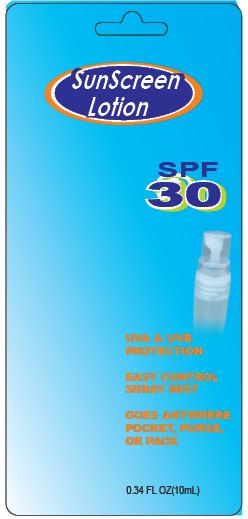 DRUG LABEL: SunScreen SPF30
NDC: 31190-200 | Form: LOTION
Manufacturer: Shanghai Kejing Cleaning Products Co., Ltd.
Category: otc | Type: HUMAN OTC DRUG LABEL
Date: 20100415

ACTIVE INGREDIENTS: HOMOSALATE 5 mL/100 mL; OCTINOXATE 7.5 mL/100 mL; OCTISALATE 5 mL/100 mL; OXYBENZONE 4.25 mL/100 mL
INACTIVE INGREDIENTS: DIMETHICONE

SunScreen Lotion SPF30

Active ingredient Purpose

Homosalate 5 percent, Octinoxate 7.5 percent,
Octisalate 5 percent, Oxybenzone 4.25 percent............................................Sunscreen

PURPOSE

Uses: Helps prevent sunburn

Warnings: For external use only.

When using this product: Avoid contact with eyes, In case of eye contact, flush with plenty of water.

Stop use and ask a doctor if irritation or redness develops.

Keep out of reach of children. If swallowed, get medical help
or contact a Poison Control Center.

DOSAGE AND ADMINISTRATION

Directions. Apply generously and evenly before sun exposure.
Reapply as needed or after towel drying, swimming,or sweating. Ask doctor before using on children under 6 months.

Other information.
Sun Alert: Limiting sun exposure and using sunscreens may
reduce the risk of skin aging, skin cancer, and other harmful
effects of the sun.

SPF30 SUNSCREEN SPRAY

UVAand UVB PROTECTION

Distributed by Tekweld Inc.
180 Central Avenue,
FARMINGDALE,NY11735

made in China MFG:90807

Inactive ingredients: Acrylates/Octylacrylamide copolymer,
Alcohol Denat, Dimethicone, Fragrance.

PACKAGE LABEL

SPF 30

SunScreen Lotion

UVA and UVB PROTECTION

Active ingredient Purpose
Homosalate 5 percent, Octinoxate 7.5 percent,
Octisalate 5 percent, Oxybenzone 4.25 percent ..............................Sunscreen
0.34 FL OZ (10 mL)

PACKAGE LABEL

SunScreen Lotion

SPF30

UVA and UVB

PROTECTION

EASY CONTROL SPRAY MIST

GOES ANYWHERE POCKET, PURSE, OR PACK

0.34 FL OZ (10mL)